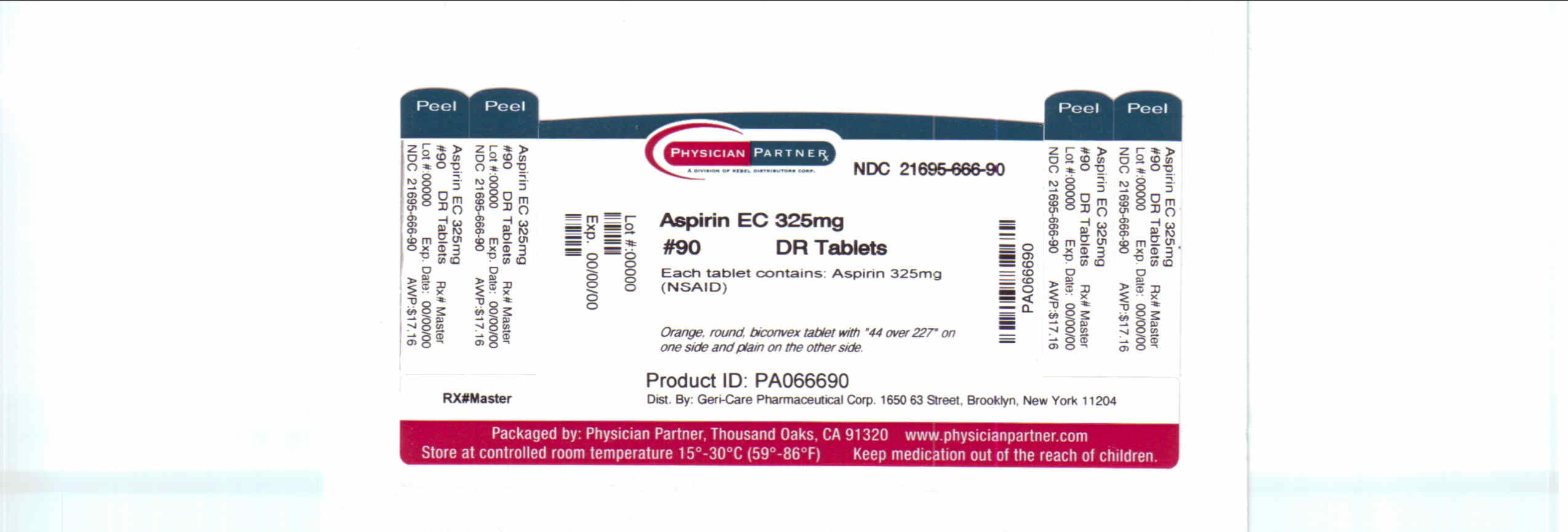 DRUG LABEL: Aspirin
NDC: 21695-666 | Form: TABLET
Manufacturer: Rebel Distributors Corp
Category: otc | Type: HUMAN OTC DRUG LABEL
Date: 20110217

ACTIVE INGREDIENTS: ASPIRIN 325 mg/1 1
INACTIVE INGREDIENTS: CELLULOSE ACETATE; CROSCARMELLOSE SODIUM; D&C YELLOW NO. 10; FD&C YELLOW NO. 6; HYPROMELLOSES; HYPROMELLOSE PHTHALATE (24% PHTHALATE, 55 CST); FERRIC OXIDE RED; METHACRYLIC ACID; MINERAL OIL; POLYDEXTROSE; POLYSORBATE 80; PROPYLENE GLYCOL; SODIUM ALGINATE; SODIUM BICARBONATE; SODIUM LAURYL SULFATE; STEARIC ACID; TALC; TITANIUM DIOXIDE; TRIACETIN; TRIETHYL CITRATE; WHITE WAX

Aspirin Drug Facts

Active ingredient

Aspirin 325mg

Purpose

Pain Reliever

Keep Out of Reach of Children

In case of overdose, get medical help or contact a Poison Control Center right away.

Uses

For the temporary relief of minor aches and pains. Ask your doctor about other uses for aspirin.

Warnings

Reye's Syndrome: Children and teenagers who have or are recovering from chicken pox or flu-like symptoms should not use this product. When using this product, if changes in behavior with nausea and vomiting occur, consult a doctor because these symptoms could be an early sign or Reye's syndrome, a rare but serious illness.

Allergy Alert: Aspirin may cause a severe allergic reaction which may include hives, facial swelling, asthma (wheezing) or shock.

Stomach bleeding warning: This product contains an NSAID, which may cause severe stomach bleeding. The chance is higher if you ° are age 60 or older ° have had stomach ulcers or bleeding problems ° take a blood thinning (anticoagulant) or steroid drug ° take other drugs containing prescription or nonprescription NSAIDs (aspirin, ibuprofen, naproxen, or others) ° have 3 or more alcoholic drinks every day while using this product ° take more or for a longer time than directed.

Do not use if you are allergic to aspirin or any other pain reliever/fever reducer.

Ask a doctor before use if ° the stomach bleeding warning applies to you ° you are taking a diuretic ° you have a history of stomach problems such as heartburn ° you have high blood pressure, heart disease, liver cirrhosis, kidney disease or asthma.

Ask a doctor or pharmacist before use if you are ° taking any other drug containing an NSAID (prescription or nonprescription) ° taking a blood thinning (anticoagulant) or steroid drug ° taking a prescription drug for diabetes, gout or arthritis.

Stop use and ask a doctor if ° you experience any of the following signs of stomach bleeding: feel faint, vomit blood, have bloody or black stools, have stomach pain that does not get better, an allergic reaction occurs. Seek medical help right away if pain gets worse or lasts more than 10 days, redness or swelling is present, fever gets worse or lasts more than 3 days, any new symptoms occur, or ringing in the ears or loss of hearing occurs.

If pregnant or breast-feeding, ask a health professional before use. It is especially important not to use aspirin during the last 3 months of pregnancy unless definitely directed to do so by a doctor because it may cause problems in the unborn child or complications during delivery.

Directions

Drink a full glass of water with each dose. Swallow whole; do not chew or crush. Do not exceed recommend dose.

Adults and children 12 years and older: take 1-2 tablets every 4 hours, as needed, not more than 12 tablets in 24 hours, or as directed by a doctor.

Children under 12: ask a doctor.

Other Information

Store at room temperature, 15°C - 30°C (59°F - 86°F).

For institutional use only.

Inactive ingredients

May contain acetylated monoglycerides, cellulose, croscarmellose sodium, D&C yellow no. 10, FD&C yellow no. 6, hypromellose, hypromellose phthalate, iron oxide, methacrylic acid, mineral oil, PEG, polydextrose, polysorbate 80, polyvinyl acetate phthalate, propylene glycol, silica sodium alginate, sodium bicarbonate, sodium lauryl sulfate, starch stearic acid, talc, titanium dioxide, triacetin, triethyl citrate, wax.